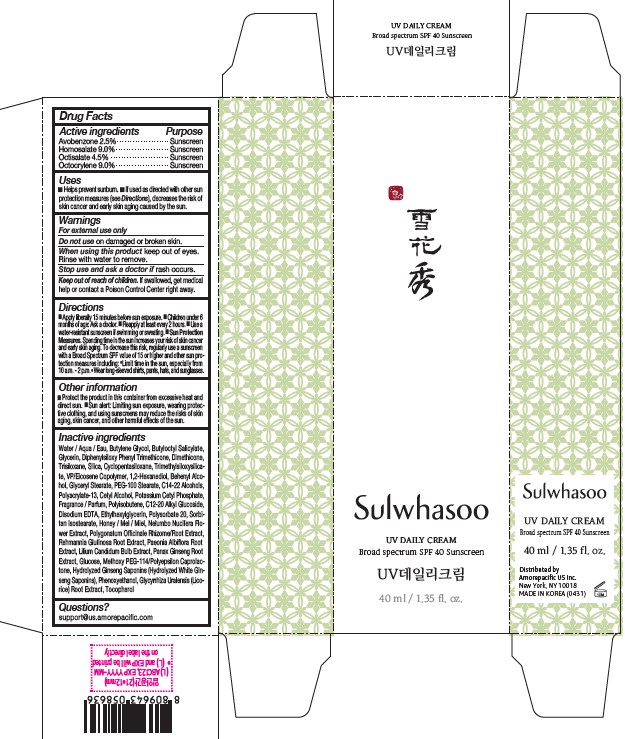 DRUG LABEL: Sulwhasoo UV Daily Cream
NDC: 43419-085 | Form: CREAM
Manufacturer: Amorepacific Corporation
Category: otc | Type: HUMAN OTC DRUG LABEL
Date: 20241011

ACTIVE INGREDIENTS: HOMOSALATE 3.6 g/40 mL; OCTISALATE 1.8 g/40 mL; AVOBENZONE 1 g/40 mL; OCTOCRYLENE 3.6 g/40 mL
INACTIVE INGREDIENTS: VINYLPYRROLIDONE/EICOSENE COPOLYMER; DIPHENYLSILOXY PHENYL TRIMETHICONE; ETHYLHEXYLGLYCERIN; POLYSORBATE 20; SORBITAN ISOSTEARATE; PAEONIA LACTIFLORA ROOT; ANHYDROUS DEXTROSE; POLYGONATUM ODORATUM ROOT; BUTYLENE GLYCOL; C14-22 ALCOHOLS; EDETATE DISODIUM; HONEY; NELUMBO NUCIFERA FLOWER; PHENOXYETHANOL; GLYCYRRHIZA URALENSIS ROOT; TOCOPHEROL; PEG-100 STEARATE; C12-20 ALKYL GLUCOSIDE; CETYL ALCOHOL; TRISILOXANE; SILICON DIOXIDE; CYCLOMETHICONE 5; BUTYLOCTYL SALICYLATE; 1,2-HEXANEDIOL; GLYCERYL MONOSTEARATE; TRIMETHYLSILOXYSILICATE (M/Q 0.8-1.0); WATER; DOCOSANOL; POTASSIUM CETYL PHOSPHATE; GLYCERIN; ASIAN GINSENG; DIMETHICONE; POLYISOBUTYLENE (45000 MW); REHMANNIA GLUTINOSA ROOT; LILIUM CANDIDUM BULB

Sulwhasoo UV Daily Cream

ACTIVE INGREDIENTS

Avobenzone 2.5%

Homosalate 9.0%

Octisalate 4.5%

Octocrylene 9.0%

PURPOSE

Sunscreen

Uses

- Helps prevent sunburn.
- If used as directed with other sun protection measures (see Directions), decreases the risk of skin cancer and early skin aging caused by the sun.

Warnings

For external use only

Do not use on damanged or broken skin.

When using this product keep out of eyes. Rinse with water to remove.

Stop use and ask a doctor if rash occurs.

Keep out of reach of children. If swallowed, get medical help or contact a Poison Control Center right away.

Direction

- Apply liberally 15 minutes before sun exposure.
- Children under 6 months of age: Ask a doctor.
- Reapply at least every 2 hours.
- Use a water-resistant sunscreen if swimming or sweating.
- Sun Protection Measures. Spending time in the sun increases your risk of skin cancer and early skin aging. To decrease this risk, regularly use a sunscreen with a Broad Spectrum SPF value of 15 or higher and other sun protection measures including: Limit time in the sun, especially from 10 a.m. - 2 p.m. Wear long-sleeved shirts, pants, hats, and sunglasses.

Other information

- Protect the product in this container from excessive heat and direct sun.
- Sun alert: Limiting sun exposure, wearing protective clothing, and using sunscreens may reduce the risks of skin aging, skin cancer, and other harmful effects of the sun.

Inactive ingredients

Water, Butylene Glycol, C12-15 Alkyl Benzoate, Cyclopentasiloxane, Phenyl Trimethicone, Cyclohexasiloxane, Glycyrrhiza Uralensis (Licorice) Root Extract, 1,2-hexanediol, Camellia Sinensis Leaf Extract, Glyceryl Stearate, Panax Ginseng Root Extract, PEG-100 Stearate, Methoxy PEG-114/polyepsilon Caprolactone, Cetearyl Alcohol, Cetyl Alcohol, Aluminum Stearate, Polyhydroxystearic Acid, PEG-40 Stearate, Alumina, Phenoxyethanol, Fragrance, Hydroxyethyl Acrylate/
sodium Acryloyldimethyl Taurate Copolymer, Polyacrylate-13, Polygonatum
Officinale Rhizome/root Extract, Rehmannia Glutinosa Root Extract, Lilium Tigrinum Flower/leaf/stem Extract, Paeonia Albiflora Root Extract, Nelumbo Nucifera Seed Extract, Stearic Acid, Chrysanthemum Morifolium Flower Extract, Citrus Unshiu Peel Extract, Xanthan Gum, Polyisobutene, Coix Lacryma-jobi Ma-yuen Seed Extract, Adenophora Stricta Root Extract, Glycerin, Ophiopogon Japonicus Root Extract, Honey, Carbomer, Polymethyl Methacrylate, Machilus Thunbergii Bark Extract, Ethylhexylglycerin, Paeonia Suffruticosa Root Extract, Lycium Chinense Root Extract, Propanediol, Angelica Tenuissima Root Extract, Disodium EDTA, Polysorbate 20, Silica, Natto Gum, Dimethicone, Beta-glucan, Triethoxycaprylylsilane, Myristic Acid, Stearyl Behenate, Polyglyceryl-3 Methylglucose Distearate, Hydroxypropyl Bispalmitamide MEA, Inulin Lauryl Carbamate

Questions?

support@us.amorepacific.com

Sulwhasoo UV Daily Cream - Carton

Sulwhasoo

SNOWISE

UV DAILY CREAM

Braod Spectrum 40 Sunscreen

40 ml / 1.35 fl. oz.